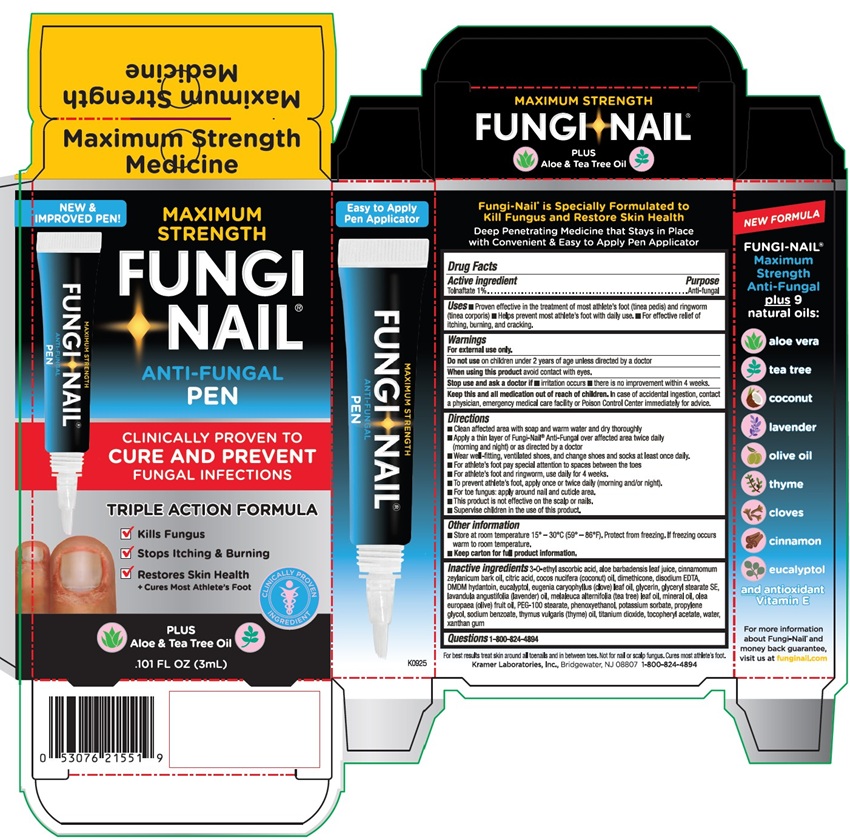 DRUG LABEL: Fungi Nail Anti-Fungal Pen
NDC: 55505-193 | Form: LIQUID
Manufacturer: Kramer Laboratories
Category: otc | Type: HUMAN OTC DRUG LABEL
Date: 20251219

ACTIVE INGREDIENTS: Tolnaftate 1 g/100 mL
INACTIVE INGREDIENTS: 3-O-Ethyl Ascorbic Acid; Aloe Vera Leaf; Cinnamomum Massoy Bark Oil; Citric Acid Monohydrate; Cocos Nucifera Whole; Dimethicone 350; Edetate Disodium; Dmdm Hydantoin; Eucalyptol; Eugenia Uniflora Leaf; Glycerin; Glyceryl Stearate Se; Lavender Oil; Tea Tree Oil; Mineral Oil; Olive Oil; Glyceryl Stearate/Peg-100 Stearate; Phenoxyethanol; Potassium Sorbate; Propylene Glycol; Docusate Sodium/Sodium Benzoate; Thyme; Titanium Dioxide; .Alpha.-Tocopherol Acetate; Water; Xanthan Gum

Drug Facts

ACTIVE INGREDIENT

Active Ingredient | Purpose
Tolnaftate 1% | Anti-fungal

Uses

■ proven effective in the treatment of most athlete's foot (tinea pedis) and ringworm (tinea corporis) ■ helps prevent most athlete's foot with daily use ■ for effective relief of itching, burning and cracking.

Warnings

For external use only

Do not use on children under 2 years of age unless directed by a doctor.

When using this product avoid contact with eyes.

Stop use and ask a doctor if

■ irritation occurs ■ there is no improvement within 4 weeks.

KEEP OUT OF REACH OF CHILDREN

Keep this and all medication out of the reach of children. In case of accidental ingestion, contact a physician, emergency medical care facility or Poison Control Center immediately for advice.

Directions

■ Clean affected area with soap and water and dry thoroughly. ■ Apply a thin layer of Fungi-Nail® Anti-Fungal over affected area twice daily (morning and night) or as directed by a doctor. ■ Wear well-fitting, ventilated shoes and change shoes and socks at least once daily. ■ For athlete's foot pay special attention to spaces between the toes. ■ For athlete's foot and ringworm, use daily for 4 weeks. ■ To prevent athlete's foot, apply once or twice daily (morning and/or night). ■ For toe fungus: apply around nail and cuticle area. ■ The product is not effective on the scalp or nails. ■ Supervise children in the use of this product.

Other information
■ Store at room temperature 15°-30°C (59°-86°F). Protect from freezing. If freezing occurs warm to room temperature. ■ Keep carton for full product information.

INACTIVE INGREDIENT

Inactive ingredients 3-0-ethyl ascorbic acid, aloe barbadensis leaf juice, cinnamomum zeylanicum bark oil, citric acid, cocos nucifera (coconut) oil, dimethicone, disodium EDTA, DMDM hydantoin, eucalyptol, eugenia caryophyllus (clove) leaf oil, glycerin, glyceryl stearate SE, lavandula angustifolia (lavender) oil, melaleuca alternifolia (tea tree) leaf oil, mineral oil, olea europaea (olive) fruit oil, PEG-100 stearate, phenoxyethanol, potassium sorbate, propylene glycol, sodium benzoate, thymus vulgaris (thyme) oil, titanium dioxide, tocopheryl acetate, water, xanthan gum

Questions

1-800-824-4894

PRINCIPAL DISPLAY PANEL

Maximum Strength
Medicine
NEW &
IMPROVED PEN!
MAXIMUM
STRENGTH
FUNG
I-NAIL®
ANTI-FUNGAL
PEN
CLINICALLY PROVEN TO
CURE AND PREVENT
FUNGAL INFECTIONS
TRIPLE ACTION FORMULA
✓ Kills Fungus
✓ Stops Itching & Burning
✓ Restores Skin Health
+ Cures Most Athlete's Foot
CLINICALLY PROVEN
INGREDIENT
PLUS
Aloe & Tea Tree Oil
.101 FL OZ (3ml)
Easy to Apply
Pen Applicator
K0925
NEW FORMULA
FUNGI-NAIL®
Maximum
Strength
Anti-Fungal
plus 9
natural oils:
○ aloe vera
○ tea tree
○ coconut
○ lavender
○ olive oil
○ thyme
○ cloves
○ cinnamon
○ eucalyptol
and antioxidant
Vitamin E
For more information
about Fungi-Nail® and
money back guarantee,
visit us at funginail.com
For best results treat skin around all toenails and in between toes. Not for nail or scalp fungus, Cures most athlete's foot.
Kramer Laboratories, Inc., Bridgewater, NJ 08807 1-800-824-4894